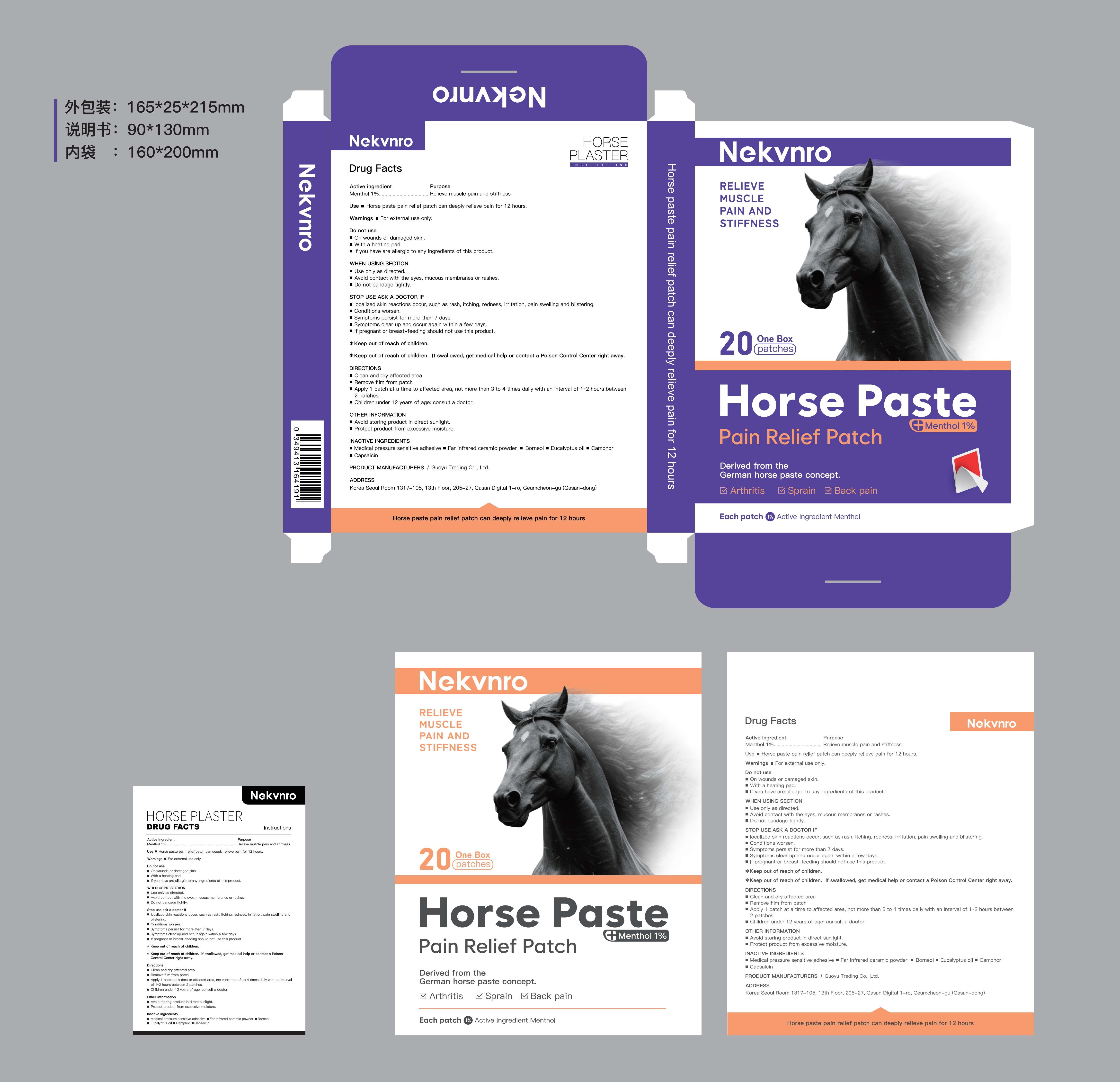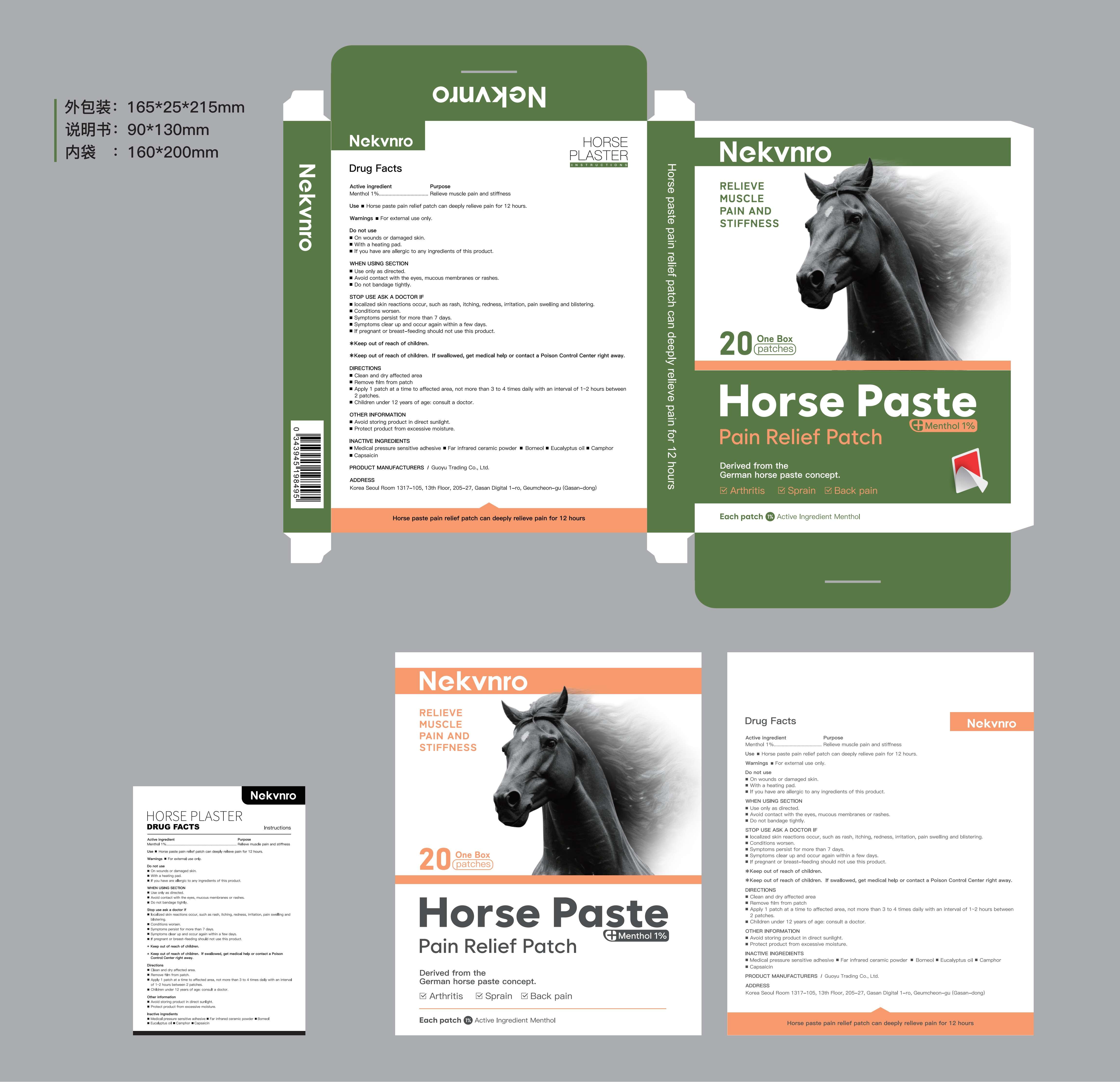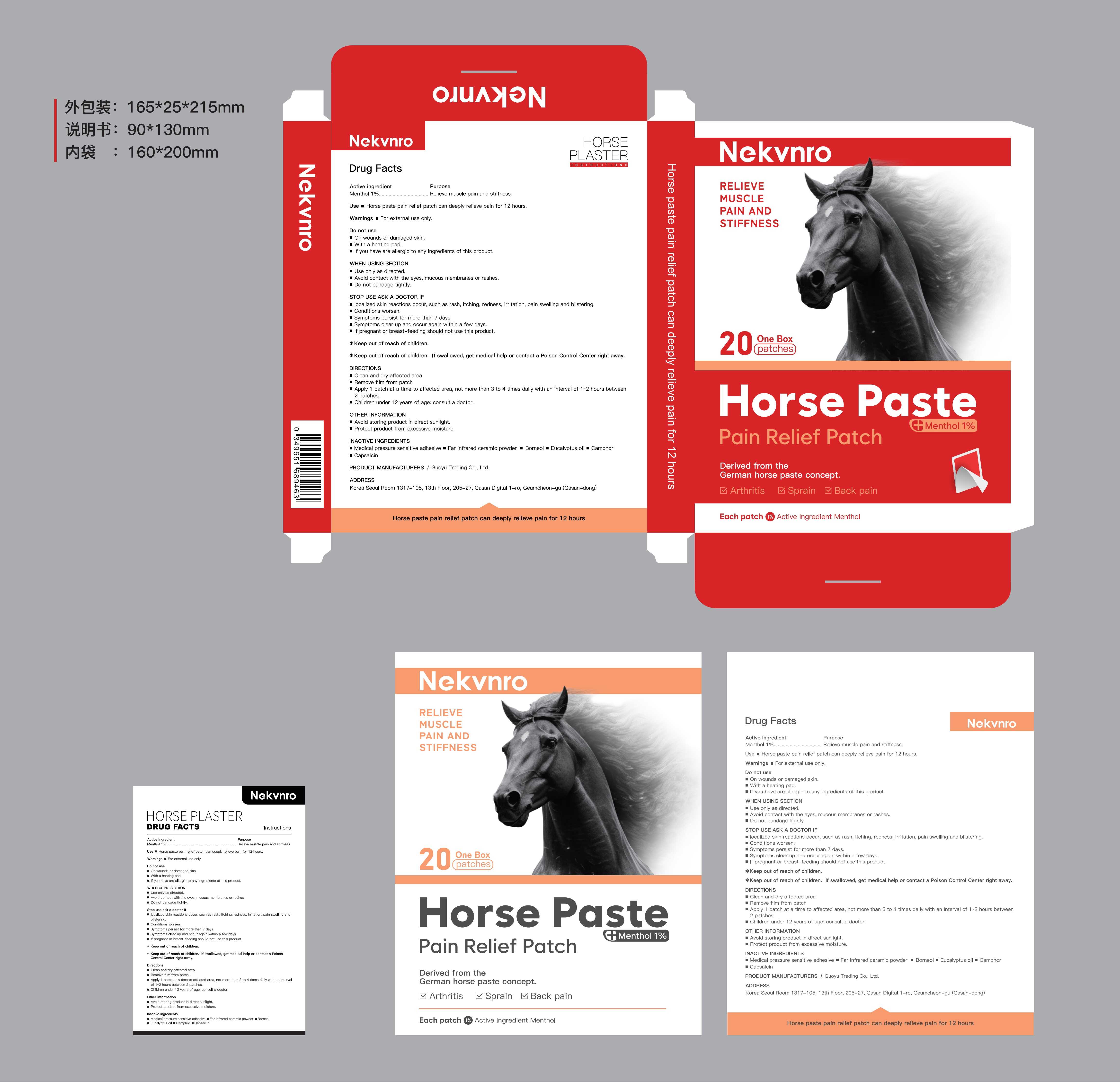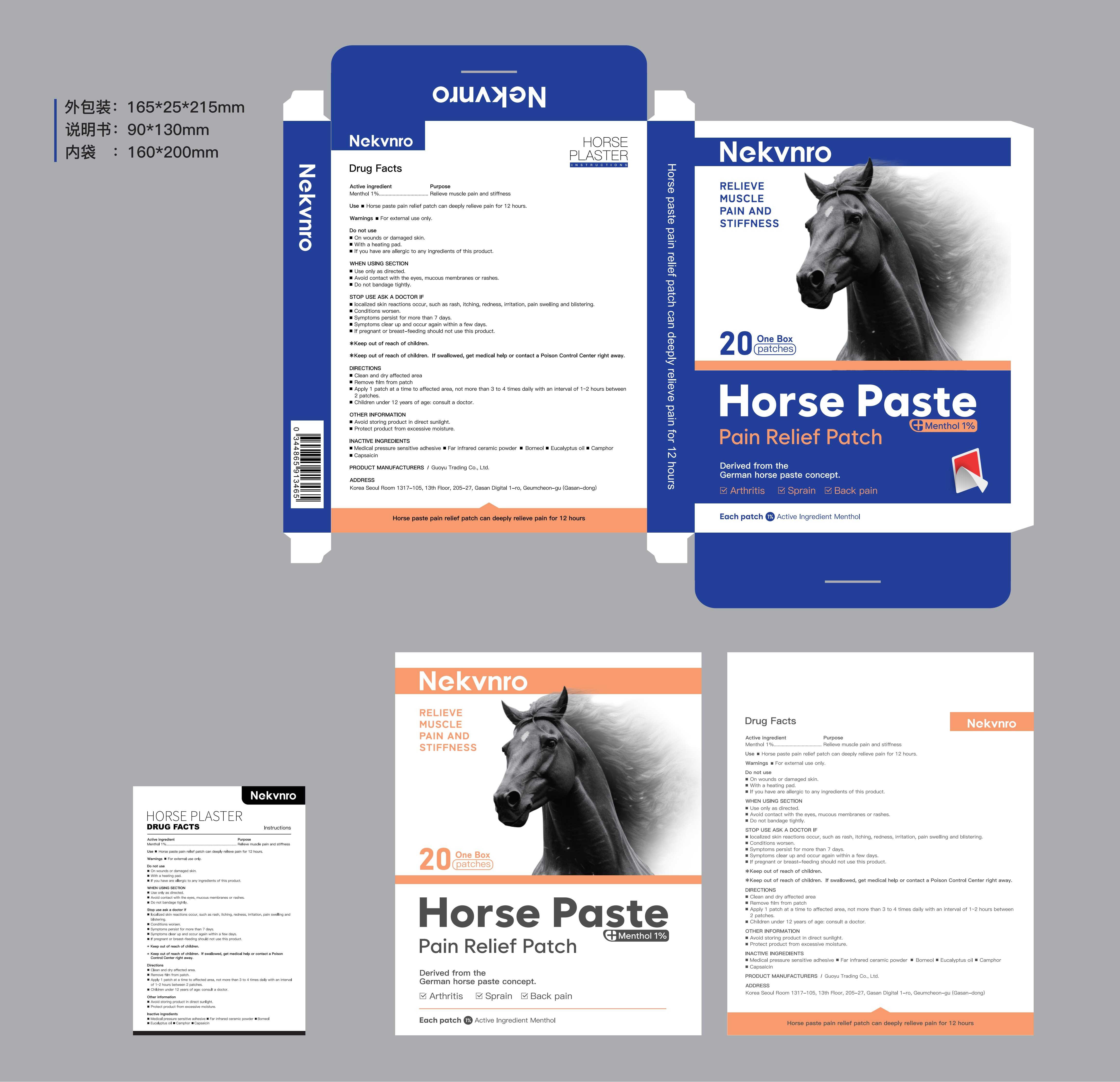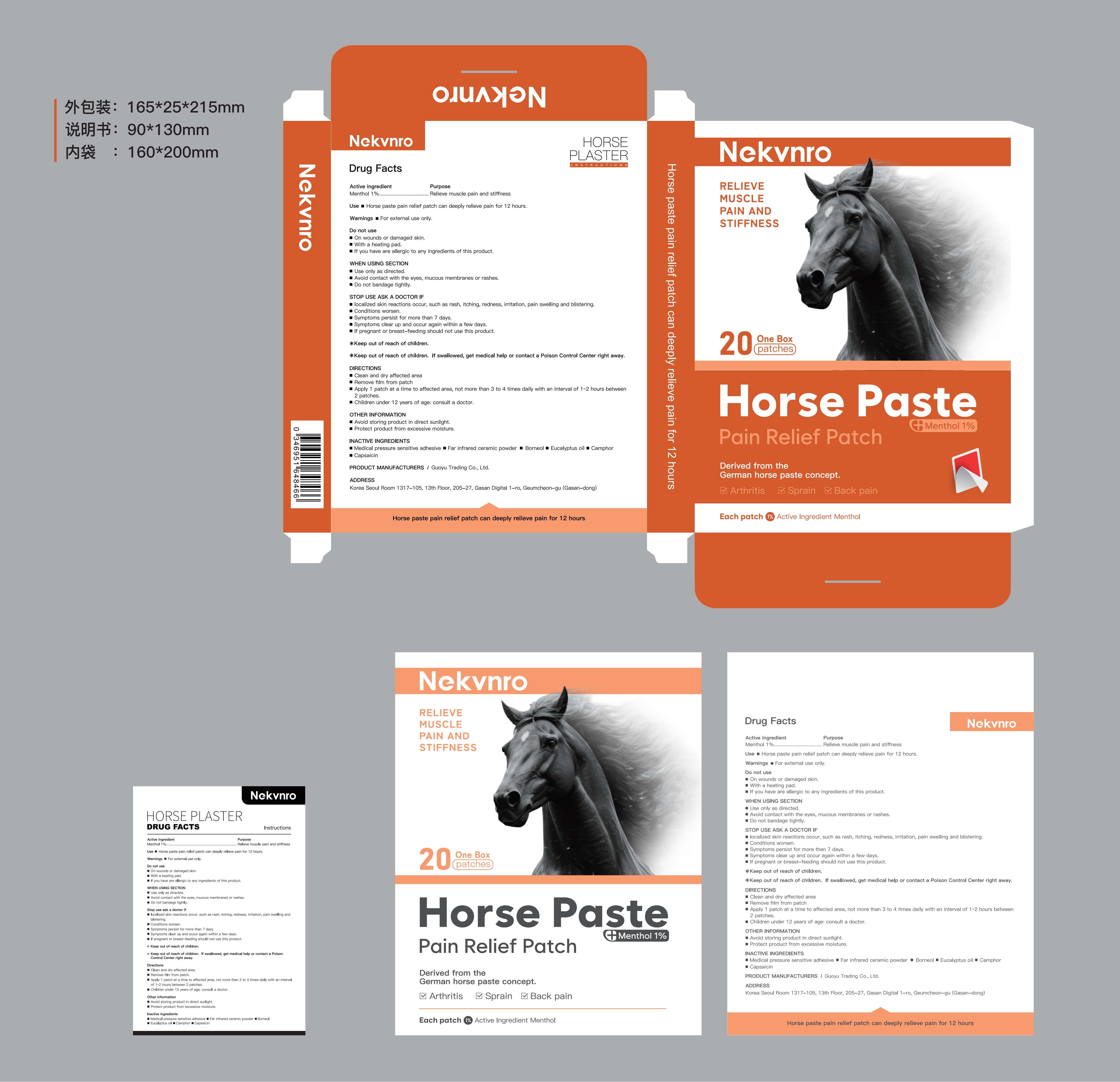 DRUG LABEL: Nekvnro Horse Paste. Pain Relief Patch
NDC: 84844-008 | Form: PATCH
Manufacturer: Guoyu Trading Co., Ltd.
Category: otc | Type: HUMAN OTC DRUG LABEL
Date: 20241104

ACTIVE INGREDIENTS: MENTHOL 1 g/100 1
INACTIVE INGREDIENTS: SPANISH SARDINE; BORNEOL; CAMPHORIC ACID, (-)-; EUCALYPTUS OIL; CAPSAICIN; SILICON DIOXIDE

84844-008

Active Ingredient

Menthol 1%

Purpose

Relieve muscle pain and stiffness

Use

Horse paste pain relief patch can deeply relieve pain for 12 hours

Warnings

For external use only

Do not use

■ on wounds or damaged skin
■ with a heating pad
■ if you have are allergic to any ingredients of this product

When Using

■ use only as directed
■ avoid contact with the eyes, mucous membranes or rashes
■ do not bandage tightly

Stop Use

■ localized skin reactions occur, such as rash, itching, redness, irritation, pain swelling and blistering
■ conditions worsen
■ symptoms persist for more than 7 days
■ symptoms clear up and occur again within a few days
If pregnant or breast-feeding should not use this product.

Ask Doctor

■ localized skin reactions occur, such as rash, itching, redness, irritation, pain swelling and blistering
■ conditions worsen
■ symptoms persist for more than 7 days
■ symptoms clear up and occur again within a few days
If pregnant or breast-feeding should not use this product.

Keep Oot Of Reach Of Children

.Keep out of reach of children. If swallowed, get medical help or contact a Poison Control Center right away.

Directions

■ clean and dry affected area
■ remove film from patch
■ apply 1 patch at a time to affected area, not more than 3 to 4 times daily with an interval of 1~2 hours between 2 patches.
Children under 12 years of age: consult a doctor

Other information

■ avoid storing product in direct sunlight
■ protect product from excessive moisture

Inactive ingredients

Medical pressure sensitive adhesive，Far infrared ceramic powder，Borneol，Eucalyptus oil，Camphor，Capsaicin.